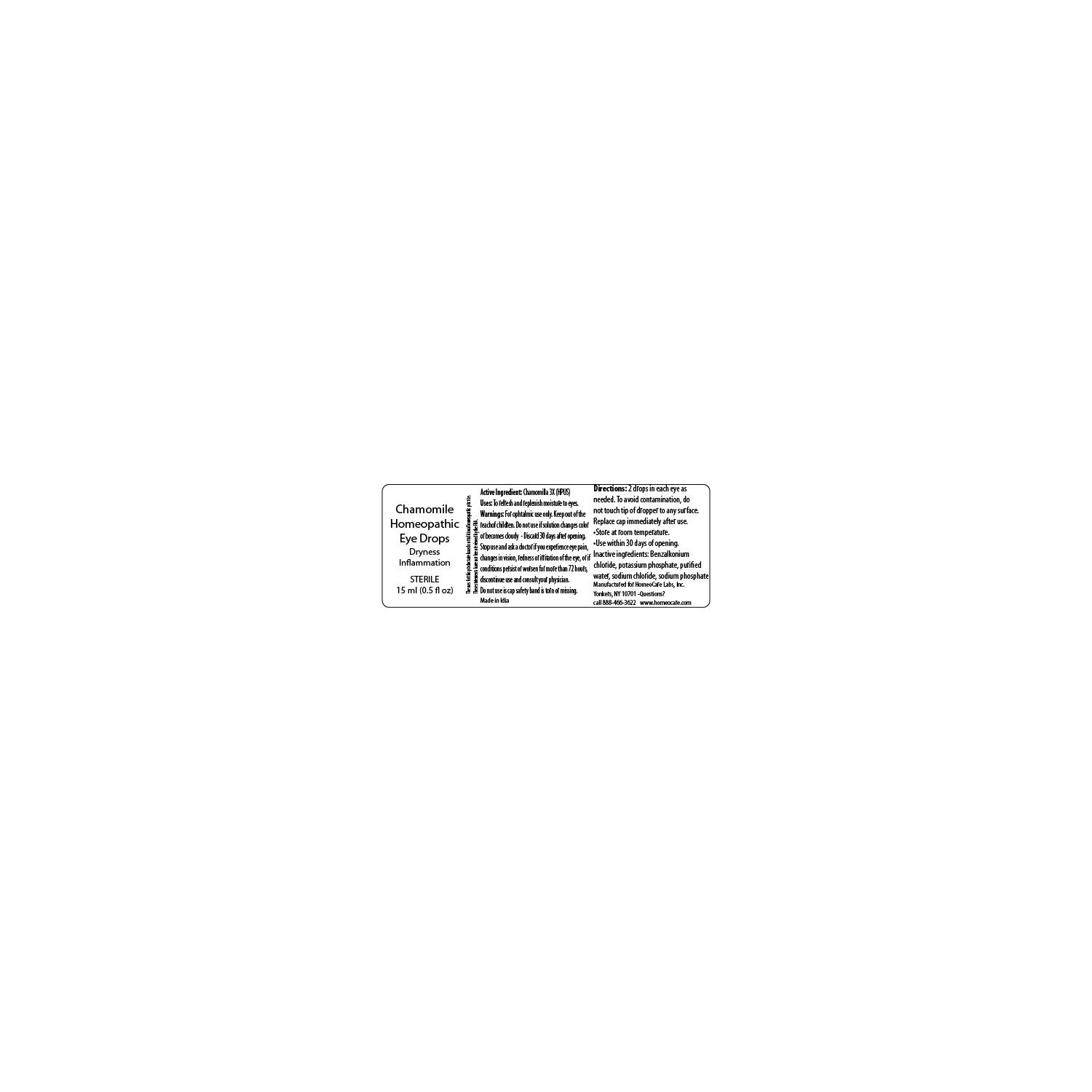 DRUG LABEL: Chamomile Homeopathic Eye Drops
NDC: 61727-354 | Form: SOLUTION/ DROPS
Manufacturer: HomeoCare Laboratories
Category: homeopathic | Type: HUMAN OTC DRUG LABEL
Date: 20200117

ACTIVE INGREDIENTS: MATRICARIA CHAMOMILLA FLOWERING TOP 3 [hp_X]/1 mL
INACTIVE INGREDIENTS: SODIUM CHLORIDE; BENZALKONIUM CHLORIDE; POTASSIUM PHOSPHATE, UNSPECIFIED FORM; SODIUM PHOSPHATE, DIBASIC; WATER

Chamomile Homeopathic Eye Drops

INACTIVE INGREDIENT

Purified water

Sodium chloride

Sodium phosphate di-basic

Potassium phosphate

Benzalkonium chloride

Purpose

Dryness

Inflammation

DOSAGE AND ADMINISTRATION

Uses to refresh and replenish moisture to eyes

Directions 2 drops in each eye as needed

To avoid contamination, do not touch tip of dropper to any surface

Replace cap immediately after use

Store at room temperature

Use within 30 days of opening

Warnings

For ophtalmic use only. Keep out of the reach of children. Do not use in solution changes color or become coudly. Discard 30 days after opening. Stop use and ask a doctor if you experience eye pain, changes in vision, redness or irritation of the eye. If condition persist or worsen for more than 72 hours, discontinue use and consult your physician.

Do not use if cap safety band is torn or missing.

Active Ingredients

Chamomilla 3X HPUS

INDICATIONS AND USAGE

Use to refresh and replenish moisture to eyes

Directions 2 drops in each eye as needed

To avoid contamination, do not touch tip of dropper to any surface

Replace cap immediately after use

Store at room temperature

Use within 30 days of opening

Keep out of the reach of children